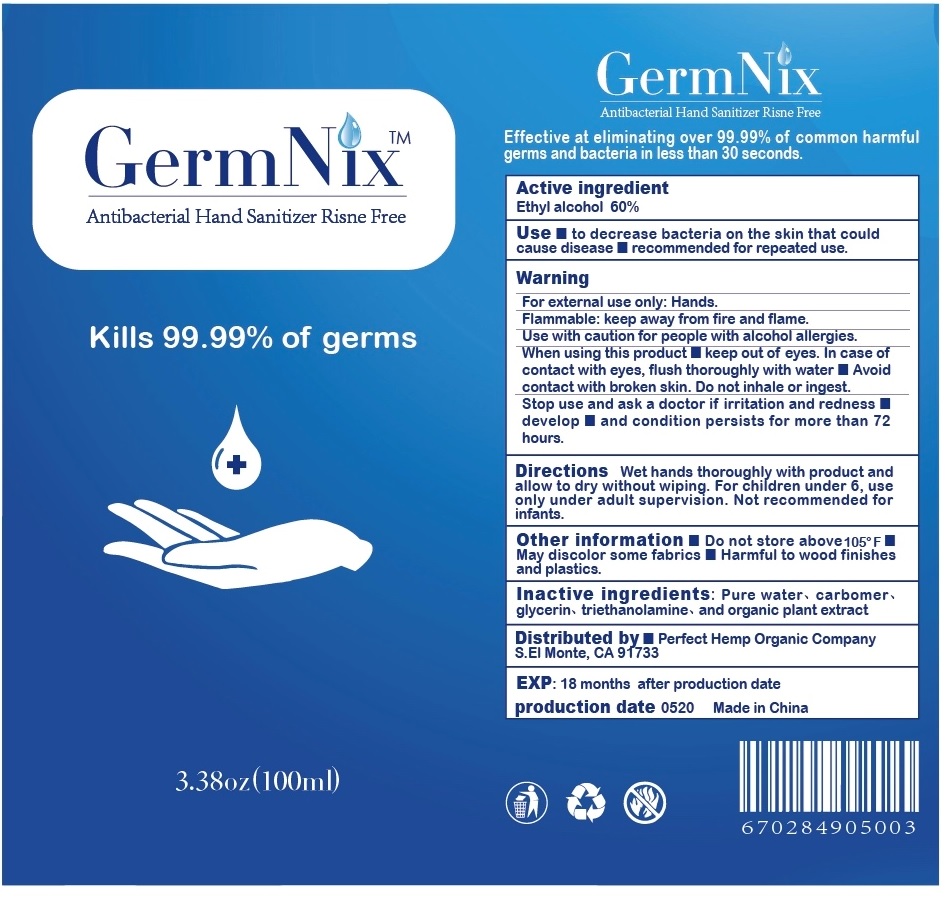 DRUG LABEL: Germ Nix Antibacterial Hand Sanitizer
NDC: 74027-100 | Form: GEL
Manufacturer: Lee's Collection Inc.
Category: otc | Type: HUMAN OTC DRUG LABEL
Date: 20200328

ACTIVE INGREDIENTS: ALCOHOL 60 mL/100 mL
INACTIVE INGREDIENTS: WATER; CARBOMER HOMOPOLYMER, UNSPECIFIED TYPE; GLYCERIN; TROLAMINE

Germ NixTM Antibacterial Hand Sanitizer

Active ingredient

Ethyl alcohol 60%

Purpose

Antiseptic

INDICATIONS AND USAGE

Use • to decrease bacteria on the skin that could cause disease • recommended for repeated use.

Warning

For external use only: Hands.

Flammable: keep away from fire and flame.

Use with caution for people with alcohol allergies.

When using this product • keep out of eyes. In case of contact with eyes, flush thoroughly with water • Avoid contact with broken skin. Do not inhale or ingest.

Stop use and ask a doctor if irritation and redness develop • and condition persists for more than 72 hours.

Keep out of reach of children.

DOSAGE AND ADMINISTRATION

Directions Wet hands thoroughly with product and allow to dry without wiping. For children under 6, use only under adult supervision. Not recommended for infants.

Other information • Do not store above 105°F • May discolor some fabrics • Harmful to wood finish and plastics.

INACTIVE INGREDIENT

Inactive ingredients: Pure water, carbomer, glycerin, triethanolamine, and organic plant extract

Kills 99.99% of germs

Effective at eliminating over 99.99% of common harmful germs and bacteria in less than 15 seconds.

Distributed by • Perfect Hemp Organic Company S.EI Monte, CA 91733

EXP: 18 months after production date

Made in China